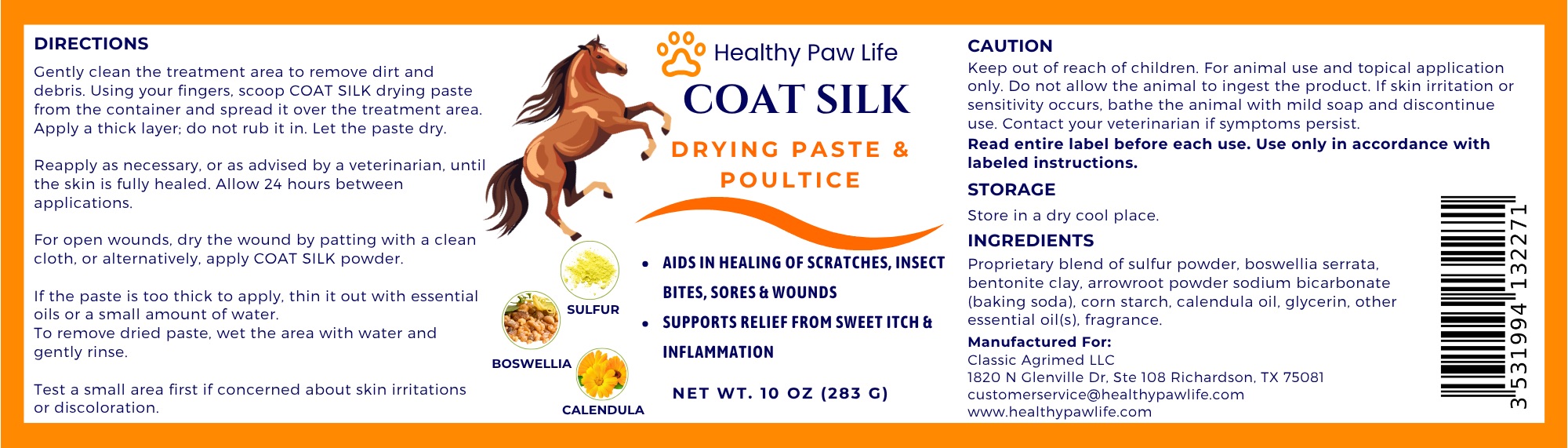 DRUG LABEL: HEALTHY PAW LIFE COAT SILK DRYING
NDC: 86130-907 | Form: PASTE
Manufacturer: CLASSIC AGRIMED LLC
Category: animal | Type: OTC ANIMAL DRUG LABEL
Date: 20250615

ACTIVE INGREDIENTS: SULFUR 3 g/100 g

HEALTHY PAW LIFE COAT SILK DRYING PASTE & POULTICE

COAT SILK DRYING PASTE & POULTICE:

Aids in healing of scratches, insect bites, sores & wounds
Supports relief from sweet itch & inflammation

Directions:

Gently clean the treatment area to remove dirt and debris. Using your fingers, scoop COAT SILK drying paste from the container and spread it over the treatment area. Apply a thick layer; do not rub it in. Let the paste dry.

Reapply as necessary, or as advised by a veterinarian, until the skin is fully healed. Allow 24 hours between applications.

For open wounds, dry the wound by patting with a clean cloth, or alternatively, apply COAT SILK powder.

If the paste is too thick to apply, thin it out with essential oils or a small amount of water.
To remove dried paste, wet the area with water and gently rinse.

Test a small area first if concerned about skin irritations or discoloration.

Caution:

Keep out of reach of children. For animal use and topical application only. Do not allow the animal to ingest the product. If skin irritation or sensitivity occurs, bathe the animal with mild soap and discontinue use. Contact your veterinarian if symptoms persist.

Read entire label before each use. Use only in accordance with labeled instructions.

Storage:

Store in a dry cool place.